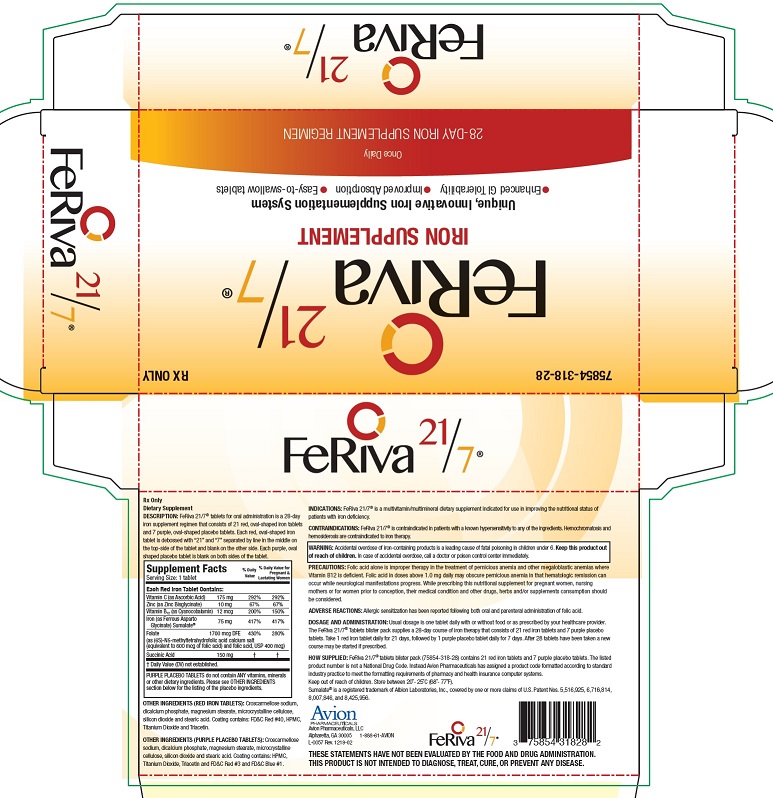 DRUG LABEL: FeRiva 21 7
NDC: 75854-318 | Form: TABLET
Manufacturer: Avion Pharmaceuticals, LLC
Category: other | Type: DIETARY SUPPLEMENT
Date: 20210107

ACTIVE INGREDIENTS: ASCORBIC ACID 175 mg/1 1; ZINC GLYCINATE 10 mg/1 1; CYANOCOBALAMIN 12 ug/1 1; FERROUS ASPARTO GLYCINATE 75 mg/1 1; FOLIC ACID 1 mg/1 1; SUCCINIC ACID 150 mg/1 1
INACTIVE INGREDIENTS: ANHYDROUS DIBASIC CALCIUM PHOSPHATE; MICROCRYSTALLINE CELLULOSE; STEARIC ACID; SILICON DIOXIDE; MAGNESIUM STEARATE; CROSCARMELLOSE SODIUM; HYPROMELLOSE, UNSPECIFIED; TITANIUM DIOXIDE; TRIACETIN; FD&C RED NO. 3; FD&C RED NO. 40; FD&C BLUE NO. 1

FeRiva 21/7
Rx Only
Dietary Supplement

STATEMENT OF IDENTITY

DESCRIPTION
FeRiva 21/7® tablets for oral administration is a 28-day iron supplement regimen that consists of 21 red, oval-shaped iron tablets and 7 purple, oval-shaped placebo tablets. Each red, oval-shaped iron tablet is debossed with “21” and “7” separated by a line in the middle on the top-side of the tablet and blank on the other side. Each purple, oval shaped placebo tablet is blank on both sides of the tablet.

Supplement Facts Serving Size: 1 tablet |  | % Daily Value | % Daily Value for Pregnant & Lactating Women
Each Red Iron Tablet Contains:
Vitamin C (as Ascorbic Acid) | 175 mg | 292% | 292%
Zinc (as Zinc Bisglycinate) | 10 mg | 67% | 67%
Vitamin B12 (as Cyanocobalamin) | 12 mcg | 200% | 150%
Iron (as Ferrrous Asparto Glycinate) Sumalate® | 75 mg | 417% | 417%
Folate (as ((6S)-N5-methyltetrahydrofolic acid calcium salt (molar equivalent to 600 mcg of folic acid) and folic acid, USP 400 mcg) | 1 mg | 250% | 125%
Succinic Acid | 150 mg | † | †
† Daily Value (DV) not established.
PURPLE PLACEBO TABLETS do not contain ANY vitamins, minerals or other dietary ingredients. Please see OTHER INGREDIENTS section below for the listing of the inert ingredients.

OTHER INGREDIENTS (RED IRON TABLETS)
Croscarmellose sodium, dicalcium phosphate, magnesium stearate, microcrystalline cellulose, silicon dioxide, and stearic acid. Coating contains: FD&C Red #40, HMPC, titanium dioxide and triacetin.

OTHER INGREDIENTS (PURPLE PLACEBO TABLETS)
Croscarmellose sodium, dicalcium phosphate, magnesium stearate, microcrystalline cellulose, silicon dioxide, and stearic acid. Coating contains: HMPC, titanium dioxide, triacetin, and FD&C Red #3, FD&C Blue #1.

INDICATIONS
FeRiva 21/7® is a multivitamin/multimineral dietary supplement indicated for use in improving the nutritional status of patients with iron deficiency.

CONTRAINDICATIONS
FeRiva 21/7® is contraindicated in patients with a known hypersensitivity to any of the ingredients. Hemochromatosis and hemosiderosis are contraindicated to iron therapy.

WARNING

Accidental overdose of iron-containing products is a leading cause of fatal poisoning in children under 6. KEEP THIS PRODUCT OUT OF REACH OF CHILDREN. In case of accidental overdose, call a doctor or poison control center immediately.

PRECAUTIONS

Folic acid alone is improper therapy in the treatment of pernicious anemia and other megaloblastic anemias where Vitamin B12 is deficient. Folic acid in doses above 1.0 mg daily may obscure pernicious anemia in that hematologic remission can occur while neurological manifestations progress. While prescribing this nutritional supplement for pregnant women, nursing mothers or for women prior to conception, their medical condition and other drugs, herbs and/or supplements consumption should be considered.

ADVERSE REACTIONS
Allergic sensitization has been reported following both oral and parenteral administration of folic acid.

DOSAGE AND ADMINISTRATION

Usual dosage is one tablet daily with or without food or as prescribed by your healthcare provider. The FeRiva 21/7® Tablets blister pack supplies a 28-day course of iron therapy that consists of 21 red iron tablets and 7 purple placebo tablets. Take 1 red iron tablet daily for 21 days, followed by 1 purple placebo tablet daily for 7 days. After 28 tablets have been taken a new course may be started if prescribed.

HOW SUPPLIED

FeRiva 21/7® tablets blister pack (75854-318-28) contains 21 red iron tablets and 7 purple placebo tablets. The listed product number is not a National Drug Code. Instead Avion Pharmaceuticals has assigned a product code formatted according to standard industry practice to meet the formatting requirements of pharmacy and health insurance computer systems.

Keep out of reach of children. Store between 20°- 25°C (68°- 77°F).

Sumalate® is a registered trademark of Albion Laboratories, Inc., covered by one or more claims of U.S. Patent Nos. 6,716,814, 8,007,846, and 8,425,956.

Avion Pharmaceuticals, LLC
Alpharetta, GA 30022
1-888-61-AVION L-0057 Rev. 1219-02

PRINCIPAL DISPLAY PANEL - 28 tablet container label

75854-318-28 RX ONLY

FeRiva 21/7

IRON SUPPLEMENT

Unique, Innovative Iron Supplementation System
• Enhanced GI Tolerability • Improved Absorption • Easy-to-swallow tablets

Once Daily
28-DAY IRON SUPPLEMENT REGIMEN

Avion
PHARMACEUTICALS